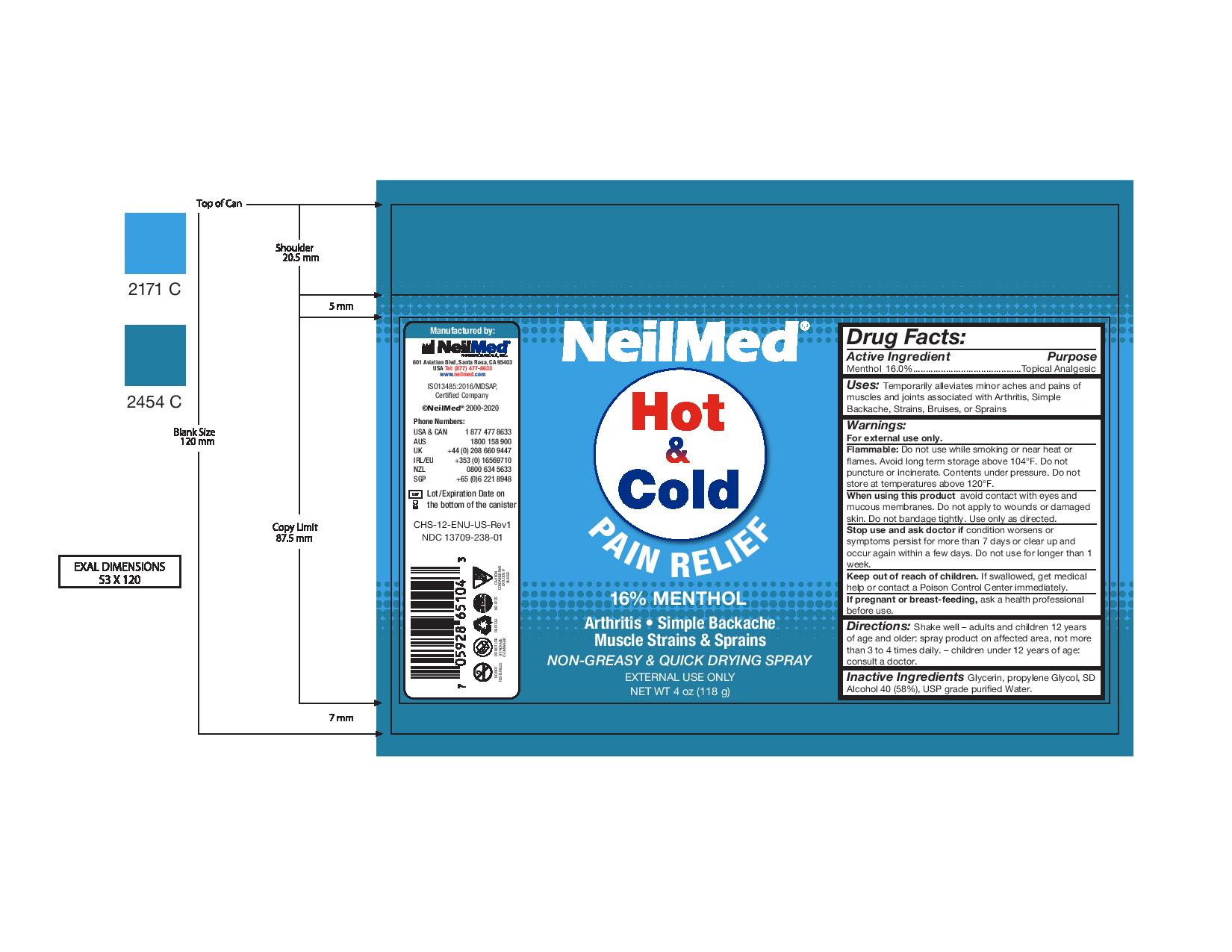 DRUG LABEL: NeilMed Hot and Cold Pain Relief
NDC: 13709-238 | Form: SPRAY
Manufacturer: NeilMed Pharmaceuticals Inc.
Category: otc | Type: HUMAN OTC DRUG LABEL
Date: 20240111

ACTIVE INGREDIENTS: MENTHOL 0.16 g/1 g
INACTIVE INGREDIENTS: ALCOHOL; PROPYLENE GLYCOL; GLYCERIN

NeilMed Hot and Cold Pain Relief Spray

Directions

Directions: Shake well – adults and children 12 years of age and older: spray product on affected area, not more than 3 to 4 times daily. – children under 12 years of age: consult a doctor.

Warnings

For external use only.
Flammable: Do not use while smoking or near heat or flames. Avoid long term storage above 104°F. Do not puncture or incinerate. Contents under pressure. Do not store at temperatures above 120°F.
When using this product avoid contact with eyes and mucous membranes. Do not apply to wounds or damaged skin. Do not bandage tightly. Use only as directed.
Stop use and ask doctor if condition worsens or symptoms persist for more than 7 days or clear up and occur again within a few days. Do not use for longer than 1 week.
Keep out of reach of children. If swallowed, get medical help or contact a Poison Control Center immediately.
If pregnant or breast-feeding, ask a health professional before use.

Inactive Ingredients

Glycerin, Propylene Glycol, SD Alcohol 40 (58%), USP grade Purified Water.

Uses

Temporarily alleviates minor aches and pains of muscles and joints associated with Arthritis, Simple Backache, Strains, Bruises, or Sprains

Warnings: Keep out of reach of children.

If swallowed, get medical help or contact a Poison Control Center immediately.

Drug Facts:

Topical Analgesic

Drug Facts:

Active Ingredient

Menthol 16.0%